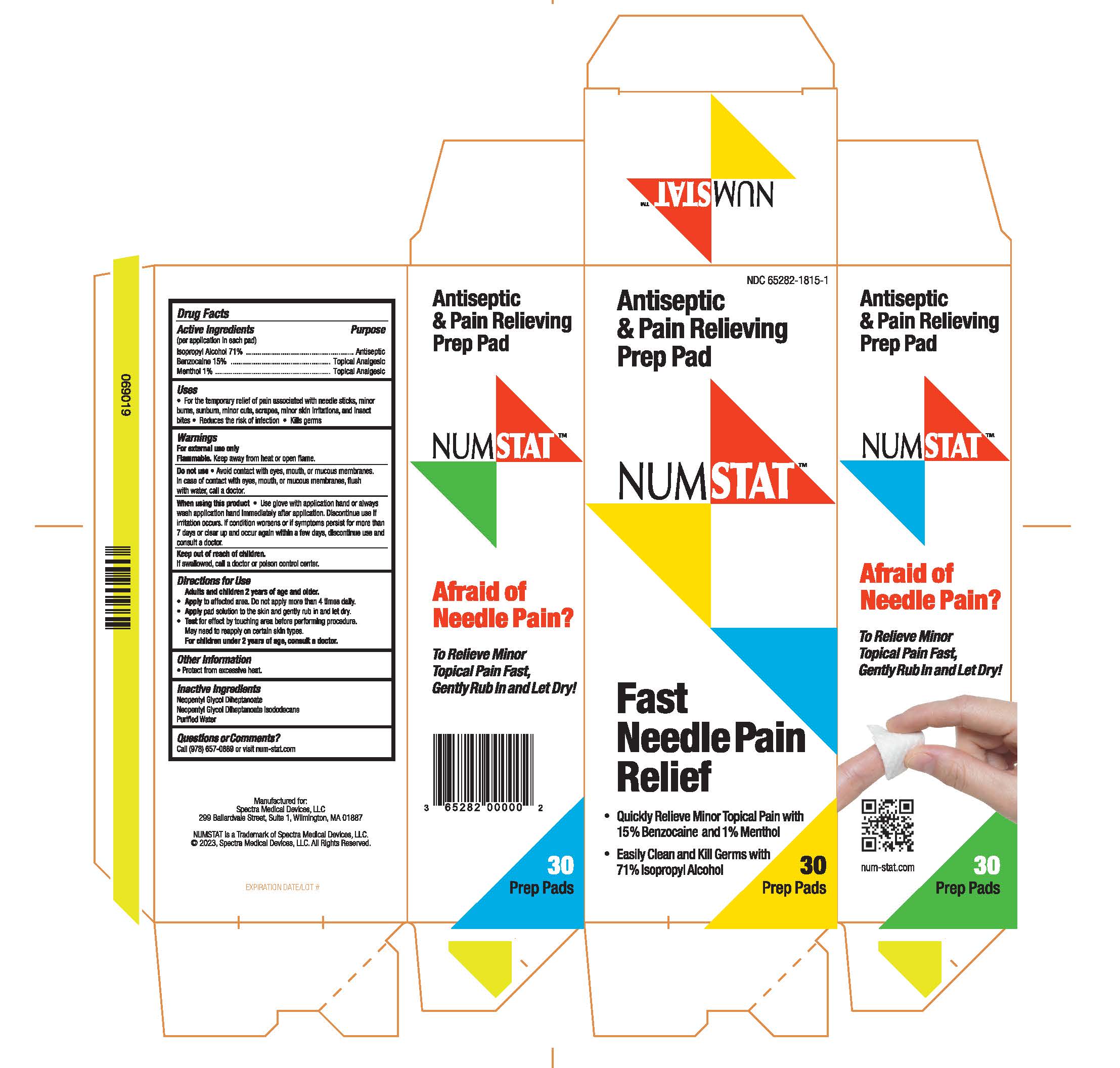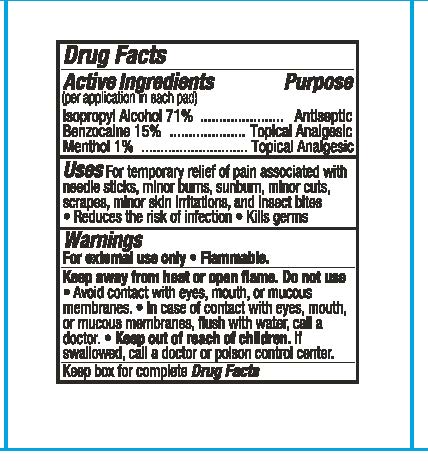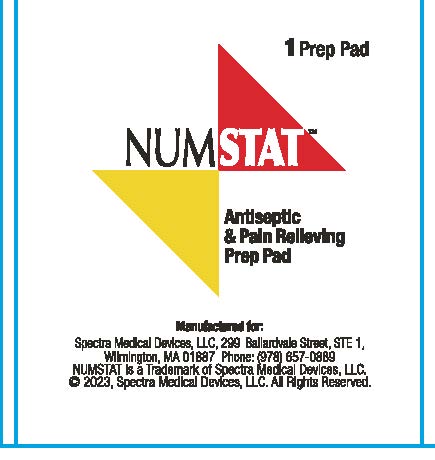 DRUG LABEL: NUMSTAT Antiseptic and Pain Relieving Prep Pad
NDC: 65282-1815 | Form: SWAB
Manufacturer: Spectra Medical Devices, LLC
Category: otc | Type: HUMAN OTC DRUG LABEL
Date: 20231220

ACTIVE INGREDIENTS: BENZOCAINE 15 g/100 g; ISOPROPYL ALCOHOL 71 g/100 g; MENTHOL 1 g/100 g
INACTIVE INGREDIENTS: WATER

Antiseptic & Pain Relieving Prep Pad

Active Ingredients

Active Ingredients (per application in each pad)

Percent Purpose

Isopropyl Alcohol................................. 71% Antiseptic

Benzocaine......................................... 15% Topical Analgesic

Menthol.............................................. 1% Topical Analgesic

Purpose

Antiseptic & Pain Relieving

Uses

• For the temporary relief of pain associated with needle sticks, minor

burns, sunburn, minor cuts, scrapes, minor skin irritations, and insect

bites • Reduces the risk of infection • Kills germs

Warnings

Flammable. Keep away from heat or open flame.

When using this product• Use glove with application hand or always wash application hand immediately after application

For external use only

Do not use• Avoid contact with eyes, mouth, or mucous membranes.

In case of contact with eyes, mouth, or mucous membranes, flush

with water, call a doctor.

Stop use

Discontinue use if irritation occurs. If condition worsens or if symptoms persist for more than 7 days or clear up and occur again within a few days, discontinue use and consult a doctor.

Keep out of reach of children. If swallowed, call a doctor or poison control center.

Directions

Directions for Use

Adults and children 2 years of age and older.

• Apply to affected area. Do not apply more than 4 times daily.

• Apply pad solution to the skin and gently rub in and let dry.

• Test for effect by touching area before performing procedure

May need to reapply on certain skin types.

For children under 2 years of age, consult a doctor.

Other Information

• Protect from excessive heat.

Inactive Ingredients

Neopentyl Glycol Diheptanoate

Neopentyl Glycol Diheptanoate Isododecane

Purified Water

Questions or Comments?

Call (978) 657-0889 or visit num-stat.com

Carton Information

Antiseptic & Pain Relieving Prep Pad

NUMSTAT

Fast Needle Pain Relief

• Quickly Relieve Minor Topical Pain with 15% Benzocaine and 1% Menthol

• Easily Clean and Kill Germs with 71% Isopropyl Alcohol

Afraid of Needle Pain?

To Relieve Minor

Topical Pain Fast,

Gently Rub In and Let Dry!

Manufactured for:

Spectra Medical Devices, LLC

299 Ballardvale Street, Suite 1, Wilmington, MA 01887

NUMSTAT (TM) and © Copyright 2023

Spectra Medical Devices LLC, All Rights Reserved.

Package Label Principal Display Panel

NUMSTAT Carton